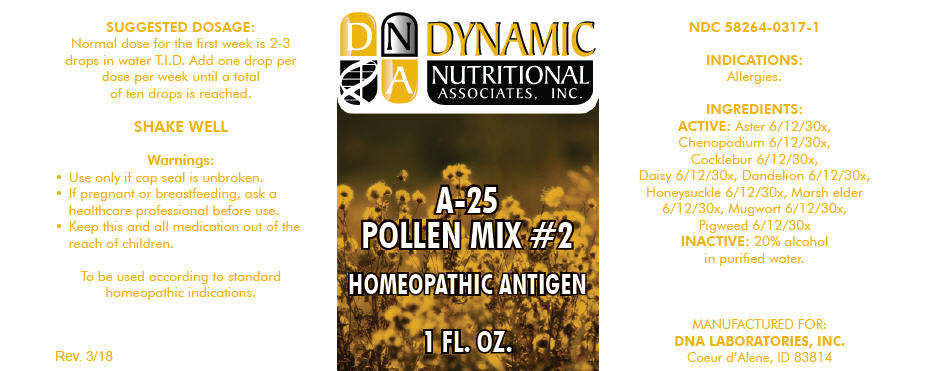 DRUG LABEL: A-25
NDC: 58264-0317 | Form: SOLUTION
Manufacturer: DNA Labs, Inc.
Category: homeopathic | Type: HUMAN OTC DRUG LABEL
Date: 20250109

ACTIVE INGREDIENTS: GRINDELIA CILIATA POLLEN 30 [hp_X]/1 mL; DYSPHANIA BOTRYS POLLEN 30 [hp_X]/1 mL; XANTHIUM STRUMARIUM POLLEN 30 [hp_X]/1 mL; LEUCANTHEMUM VULGARE POLLEN 30 [hp_X]/1 mL; TARAXACUM OFFICINALE POLLEN 30 [hp_X]/1 mL; LONICERA JAPONICA FLOWER 30 [hp_X]/1 mL; IVA ANNUA POLLEN 30 [hp_X]/1 mL; ARTEMISIA VULGARIS POLLEN 30 [hp_X]/1 mL; AMARANTHUS RETROFLEXUS POLLEN 30 [hp_X]/1 mL
INACTIVE INGREDIENTS: ALCOHOL; WATER

A-25

NDC 58264-0317-1

INDICATIONS

PURPOSE

Allergies.

INGREDIENTS

ACTIVE

Aster 6/12/30x, Chenopodium 6/12/30x, Cocklebur 6/12/30x, Daisy 6/12/30x, Dandelion 6/12/30x, Honeysuckle 6/12/30x, Marsh elder 6/12/30x, Mugwort 6/12/30x, Pigweed 6/12/30x

INACTIVE

20% alcohol in purified water.

SUGGESTED DOSAGE

Normal dose for the first week is 2-3 drops in water T.I.D. Add one drop per dose per week until a total of ten drops is reached.

STORAGE AND HANDLING

SHAKE WELL

Warnings

- Use only if cap seal is unbroken.

PREGNANCY OR BREAST FEEDING

- If pregnant or breastfeeding, ask a healthcare professional before use.

KEEP OUT OF REACH OF CHILDREN

- Keep this and all medication out of the reach of children.

To be used according to standard homeopathic indications.

PRINCIPAL DISPLAY PANEL - 1 FL. OZ. Bottle Label

DYNAMIC
NUTRITIONAL
ASSOCIATES, INC.

A-25
POLLEN MIX #2

HOMEOPATHIC ANTIGEN

1 FL. OZ.